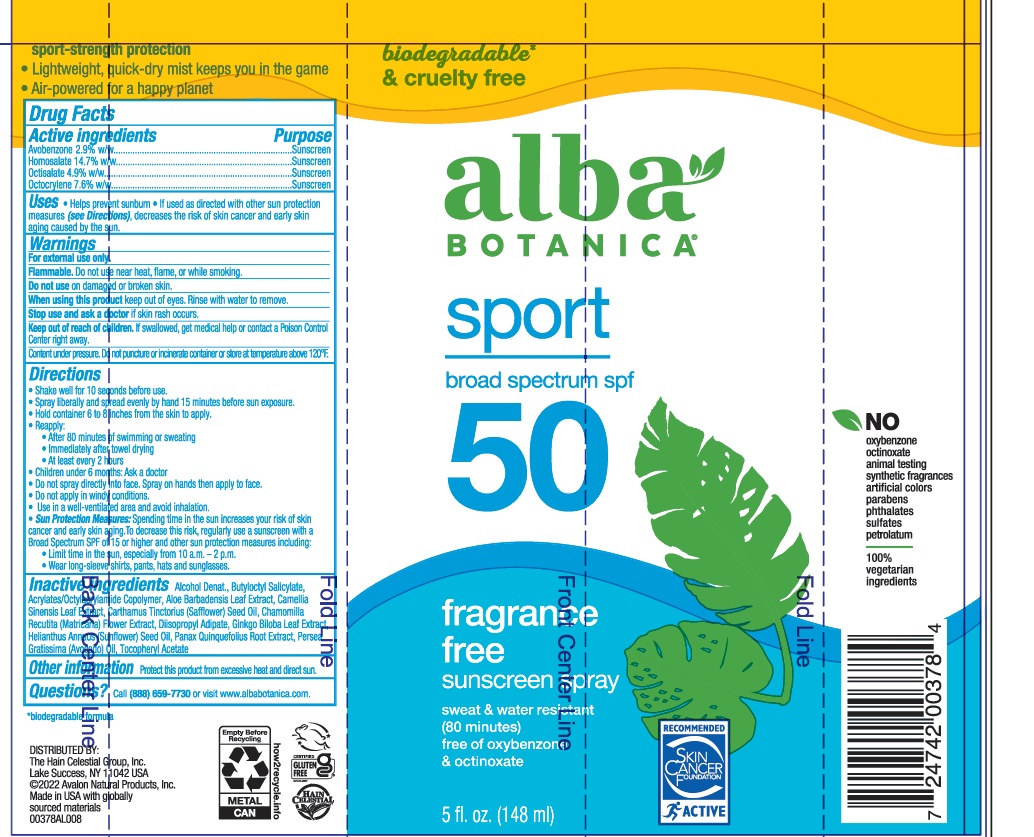 DRUG LABEL: Alba Botanica Sport SPF 50 Sunscreen
NDC: 61995-0388 | Form: SPRAY
Manufacturer: Hain Celestial Group, Inc.
Category: otc | Type: HUMAN OTC DRUG LABEL
Date: 20231116

ACTIVE INGREDIENTS: OCTOCRYLENE 7.6 g/100 mL; OCTISALATE 4.9 g/100 mL; AVOBENZONE 2.9 g/100 mL; HOMOSALATE 14.7 g/100 mL
INACTIVE INGREDIENTS: BUTYLOCTYL SALICYLATE; AMERICAN GINSENG; AVOCADO OIL; SUNFLOWER OIL; ACRYLATE/ISOBUTYL METHACRYLATE/N-TERT-OCTYLACRYLAMIDE COPOLYMER (75000 MW); ALOE VERA LEAF; ALCOHOL; GREEN TEA LEAF; SAFFLOWER OIL; CHAMOMILE; DIISOPROPYL ADIPATE; GINKGO; .ALPHA.-TOCOPHEROL ACETATE

Alba Botanica Sport SPF 50 Sunscreen Spray

ACTIVE INGREDIENT

Avobenzone 2.9%

Homosalate 14.7%

Octisalate 4.9%

Octocrylene 7.6%

PURPOSE

Sunscreen

INDICATIONS AND USAGE

Helps prevent sunburn.

If used as directed with other sun protection measures (see Directions), decreases the risk of skin cancer and early skin aging caused by the sun.

DOSAGE AND ADMINISTRATION

Apply liberally 15 minutes before sun exposure. Reapply after 80 minutes of swimming or sweating, immediately after towel drying and at least every 2 hours. Children under 6 months: ask a doctor. Sun Protection Measures: Spending time in the sun increases your risk of skin cancer and early skin aging. To decrease risk, regularly use a sunscreen with broad spectrum SPF 15 or higher and other protective measures including:

- limit time in the sun, especially from 10am to 2pm
- and wear long-sleeved shirts, pants, hats and sunglasses.

WARNINGS

For external use only. Do not use on broken or damaged skin. When using this product, keep out of eyes. Rinse with water to remove. Stop use and ask a doctor if skin rash occurs. If swallowed, get medical help or contact a Poison Control Center right away.

Keep out of reach of children. If swallowed, get medical help or contact a Poison Control Center right away.

INACTIVE INGREDIENT

Alcohol Denat., Butyloctyl Salicylate, Acrylates/Octylacrylamide Copolymer, Aloe Barbadensis Leaf Extract, Camellia Sinensis Leaf Extract, Carthamus Tinctorius (Safflower) Seed Oil, Chamomilla Recutita (Matricaria) Flower Extract, Diisopropyl Adipate, Ginkgo Biloba Leaf Extract, Helianthus Annuus (Sunflower) Seed Oil, Panax Quinquefolius Root Extract, Persea Gratissima (Avocado) Oil, Tocopheryl Acetate.